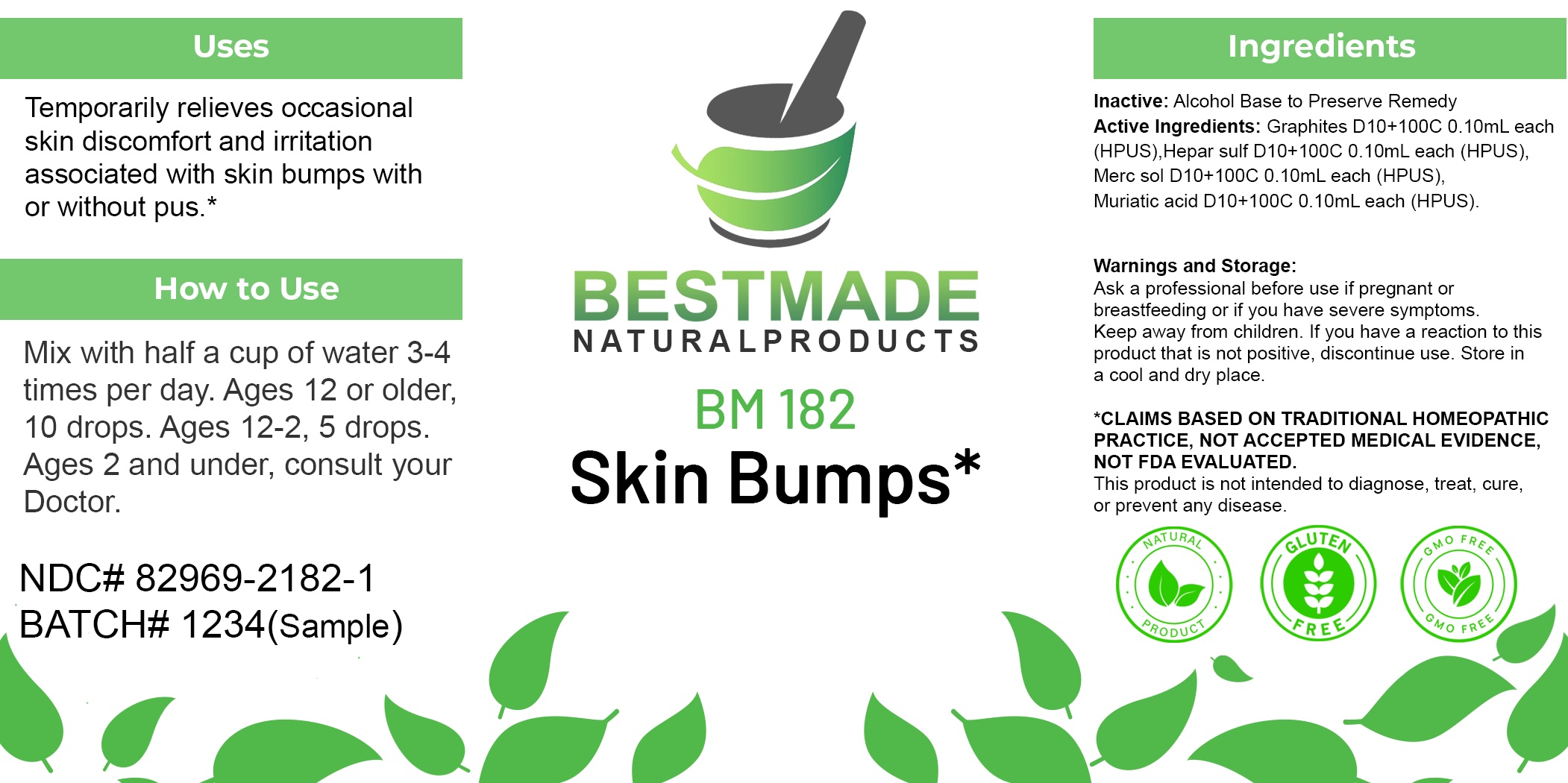 DRUG LABEL: Bestmade Natural Products BM182
NDC: 82969-2182 | Form: LIQUID
Manufacturer: Bestmade Natural Products
Category: homeopathic | Type: HUMAN OTC DRUG LABEL
Date: 20250219

ACTIVE INGREDIENTS: GRAPHITE 100 [hp_C]/100 [hp_C]; HYDROCHLORIC ACID 100 [hp_C]/100 [hp_C]; CALCIUM SULFIDE 100 [hp_C]/100 [hp_C]; MERCURIUS SOLUBILIS 100 [hp_C]/100 [hp_C]
INACTIVE INGREDIENTS: ALCOHOL 100 [hp_C]/100 [hp_C]

BM182

DOSAGE AND ADMINISTRATION

How to Use

Mix with half a cup of water 3-4 times per day. Ages 12 or older, 10 drops. Ages 12-2, 5 drops. Ages 2 and under, consult your Doctor.

Inactive:

Alcohol Base to Preserve Product

ACTIVE INGREDIENT

Active Ingredients: Graphites D10+100C 0.10mL each (HPUS), Hepar sulf D10+100C 0.10mL each (HPUS), Merc sol D10+100C 0.10mL each (HPUS), Muriatic acid D10+100C 0.10mL each (HPUS).

Uses

Temporarily relieves occasional skin discomfort and irritation associated with skin bumps with or without pus.*

*CLAIMS BASED ON TRADITIONAL HOMEOPATHIC PRACTICE, NOT ACCEPTED MEDICAL EVIDENCE, NOT FDA EVALUATED.

This product is not intended to diagnose, treat, cure, or prevent any disease.

Uses

Temporarily relieves occasional skin discomfort and irritation associated with skin bumps with or without pus.*

*CLAIMS BASED ON TRADITIONAL HOMEOPATHIC PRACTICE, NOT ACCEPTED MEDICAL EVIDENCE, NOT FDA EVALUATED.

This product is not intended to diagnose, treat, cure, or prevent any disease.

KEEP OUT OF REACH OF CHILDREN

Warnings and Storage:

Ask a professional before use if pregnant or breastfeeding or if you have severe symptoms. Keep away from children. If you have a reaction to this product that is not positive, discontinue use. Store in a cool and dry place.

Warnings and Storage:

Ask a professional before use if pregnant or breastfeeding or if you have severe symptoms. Keep away from children. If you have a reaction to this product that is not positive, discontinue use. Store in a cool and dry place.

*CLAIMS BASED ON TRADITIONAL HOMEOPATHIC PRACTICE, NOT ACCEPTED MEDICAL EVIDENCE, NOT FDA EVALUATED.

This product is not intended to diagnose, treat, cure, or prevent any disease.

Entire package label